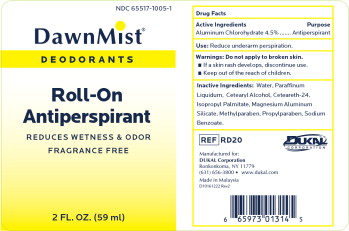 DRUG LABEL: DawnMist Antiperspirant Deodorant
NDC: 65517-1005 | Form: LIQUID
Manufacturer: Dukal LLC
Category: otc | Type: HUMAN OTC DRUG LABEL
Date: 20240723

ACTIVE INGREDIENTS: ALUMINUM CHLOROHYDRATE 45 mg/1 mL
INACTIVE INGREDIENTS: WATER; MINERAL OIL; CETOSTEARYL ALCOHOL; ISOPROPYL PALMITATE; MAGNESIUM ALUMINUM SILICATE; METHYLPARABEN; PROPYLPARABEN; SODIUM BENZOATE

DawnMist Antiperspirant Deodorant

Active Ingredient

Aluminum Chlorohydrate 4.5%

Purpose

Antiperspirant

Use

- Reduces underarm perspiration.

Warnings

For external use only.

Do not use

on broken skin.

Discontinue use if

■irritation and redness
develop ■ If condition persists for more than 72
hours consult a doctor.

Ask a doctor before use

if you have kidney disease.

Keep out of reach of children

■If swallowed, get medical help and contact Poison Control Center right away ■ Use only as directed

Directions

Apply to underarms only.

Inactive Ingredients

Water, Mineral Oil, Cetyl Alcohol, Ceteareth-24, Isopropyl Palmitate, Magnesium Aluminum Silicate, Methylparaben, Sodium Benzoate, Propylparaben